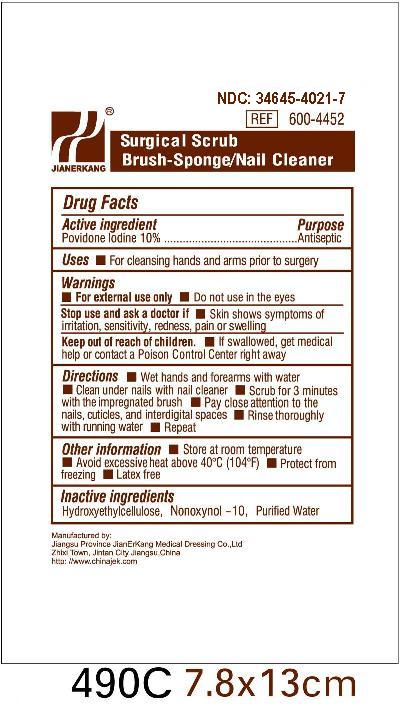 DRUG LABEL: Povidone Iodine Surgical Scrub
NDC: 34645-4021 | Form: SPONGE
Manufacturer: Jianerkang Medical Co., Ltd
Category: otc | Type: HUMAN OTC DRUG LABEL
Date: 20210329

ACTIVE INGREDIENTS: POVIDONE-IODINE 100 mg/1 mL
INACTIVE INGREDIENTS: NONOXYNOL-10; WATER

Drug Facts

Active Ingredients

Povidone Iodine 10%

Purpose

Antiseptic

Use

For cleansing hands and arms prior to surgery

Warnings

For external use only

Do not use in the eyes

Stop Use and ask a doctor if

Skin shows symptoms of irritation, sensitivity, redness, pain or swelling

Keep out of reach of children

If swallowed, get medical help or contact Poison Control Center right away

Directions

Wet hands and forearms with water

Clean under nails with nail cleaner

Scrub for 3 minutes with the impregnated brush

Pay close attention to the nails, cuticles, and interdigital spaces

Rinse thoroughly with running water

Repeat

Other Information

Store at room temperature

Avoid excessive heat above40o C (104oF)

Protect from freezing

Latex free

Inactive Ingredients

Hydroxyethylcellulose, Nonoxynol - 10, Purified Water